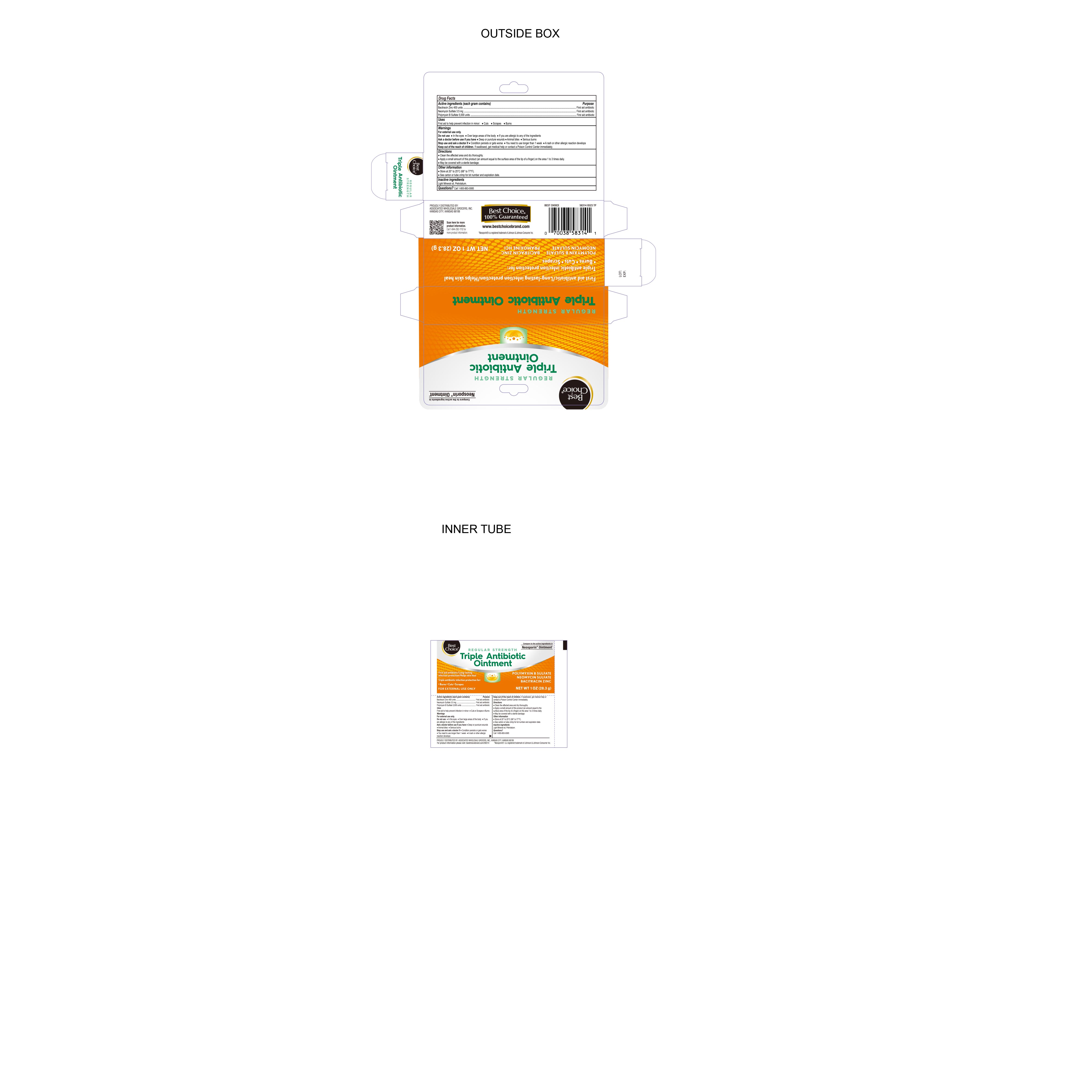 DRUG LABEL: Triple Antibiotic
NDC: 69396-131 | Form: OINTMENT
Manufacturer: TRIFECTA PHARMACEUTICALS USA LLC
Category: otc | Type: HUMAN OTC DRUG LABEL
Date: 20241231

ACTIVE INGREDIENTS: BACITRACIN ZINC 400 [USP'U]/1 g; NEOMYCIN SULFATE 3.5 mg/1 g; POLYMYXIN B SULFATE 5000 [USP'U]/1 g
INACTIVE INGREDIENTS: LIGHT MINERAL OIL; PETROLATUM

Best Choice Triple Antibiotic Ointment

Active ingredients (each gram contains)

Bacitracin zinc 400 units
Neomycin sulfate 3.5 mg
Polymyxin B sulfate 5,000 units

Purpose

First aid antibiotic

Keep out of reach of Children

If swallowed, get medical help or contact a Poison Control Center immediately.

Uses

First aid to help prevent infection in minor:● cuts ● scrapes ● burns

Warnings

For external use only.

Directions

● clean the affected area and dry thoroughly.

● apply a small amount of this product (an amount equal to the surface area of the tip of a finger) on the area 1 to 3 times daily

● may be covered with a sterile bandage.

Stop Use and Ask Doctor

- Condition persists or gets worse
- You need to use longer than 1 week
- A rash or other allergic reaction develops

Ask Doctor Before Use if you have

- Deep or puncture wounds
- Animal Bites
- Serious Burns

Do Not Use

- In the eyes
- Over large areas of the body
- If you are allergic to any of the ingredients

Inactive ingredient light Mineral Oil, Petrolatum

Other information

● store at 20° to 25°C (68° to 77°F)

● see carton or tube crimp for lot number and expiration date.

Questions? Call 1-800-883-0085

Distributed By

Proudly Distributed by

Associated Wholesale Grocers Inc.

Kansas City, Kansas 66105

For Product Information please visit: bestchoicebrands.com/58314

Neosporin is a registered trademark of Johnson & Johnson Consumer Inc.